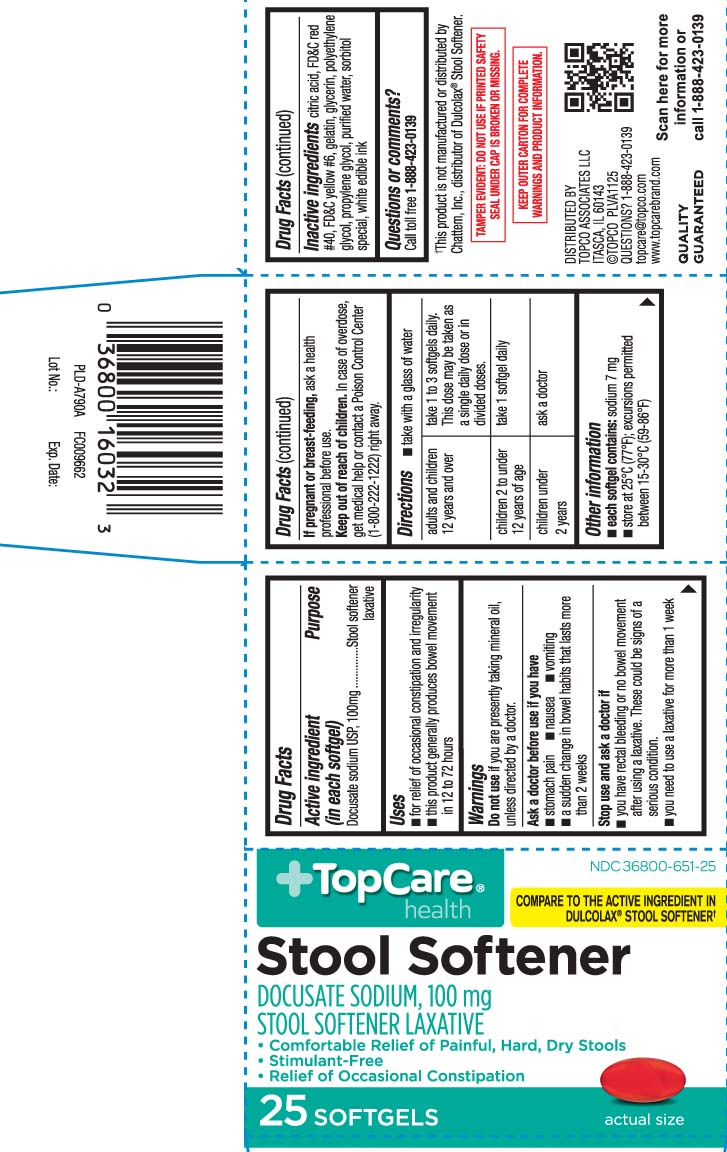 DRUG LABEL: Stool Softener
NDC: 36800-651 | Form: CAPSULE, LIQUID FILLED
Manufacturer: TOP CARE (Topco Associates LLC)
Category: otc | Type: HUMAN OTC DRUG LABEL
Date: 20260115

ACTIVE INGREDIENTS: DOCUSATE SODIUM 100 mg/1 1
INACTIVE INGREDIENTS: FD&C RED NO. 40; FD&C YELLOW NO. 6; GELATIN; POLYETHYLENE GLYCOL, UNSPECIFIED; PROPYLENE GLYCOL; WATER; SORBITOL; GLYCERIN; CITRIC ACID MONOHYDRATE; SORBITAN

DRUG FACTS

Active ingredient (in each softgel)

Docusate Sodium USP, 100 mg

Purpose

Stool softener laxative

Uses

- for relief of occasional constipation and irregularity
- this product generally produces bowel movement in 12 to 72 hours

Warnings

Do not use

if you are presently taking mineral oil, unless directed a doctor.

Ask a doctor before use if

- stomach pain
- nausea
- vomiting
- noticed a sudden change in bowel habits that lasts over 2 weeks

Stop use and ask a doctor if

- you have rectal bleeding or no bowel movement after using a laxative. These could be a sign of a serious condition.
- you need to use a stool softener laxative for more than 1 week

If pregnant or breast-feeding,

ask a health professional before use.

Keep out of reach of children.

In case of overdose, get medical help or contact a Poison Control Center (1-800-2222-1222) right away.

Directions

- take with a glass of water

adults and children 12 years and over | take 1-3 softgels daily. This dose may be taken as a single daily dose or in divided doses
children 2 to under 12 years of age | take 1 softgel daily
children under 2 years | ask a doctor

Other information

- each softgel contains: sodium 7 mg
- store at 25ºC (77ºF); excursion permitted between 15-30ºC (59-86ºF)

Inactive ingredients

citric acid, FD&C Red #40, FD&C Yellow #6, gelatin, glycerin, polyethylene glycol, propylene glycol, purified water, sorbitol special, white edible ink

Questions or comments?

Call toll free 1-888-423-0139

Principal display panel

COMPARE TO THE ACTIVE INGREDIENT IN DULCOLAX® STOOL SOFTENER†

Stool Softener

DOCUSATE SODIUM 100 mg

STOOL SOFTENER LAXATIVE

- Comfortable relief of painful, hard, dry stools
- Stimulant-free
- Relief of occasional constipation

SOFTGELS

†This product is not manufactured or distributed by Chattem, Inc., distributor of Dulcolax® Stool Softener.

TAMPER EVIDENT: DO NOT USE IF PRINTED SAFETY SEAL UNDER CAP IS BROKEN OR MISSING.

KEEP OUTER CARTON FOR COMPLETE WARNINGS AND PRODUCT INFORMATION.

DISTRIBUTED BY:

TOPCO ASSICIATES LLC

ITASCA, IL 60143

Product Label

TOPCARE HEALTH Stool Softener